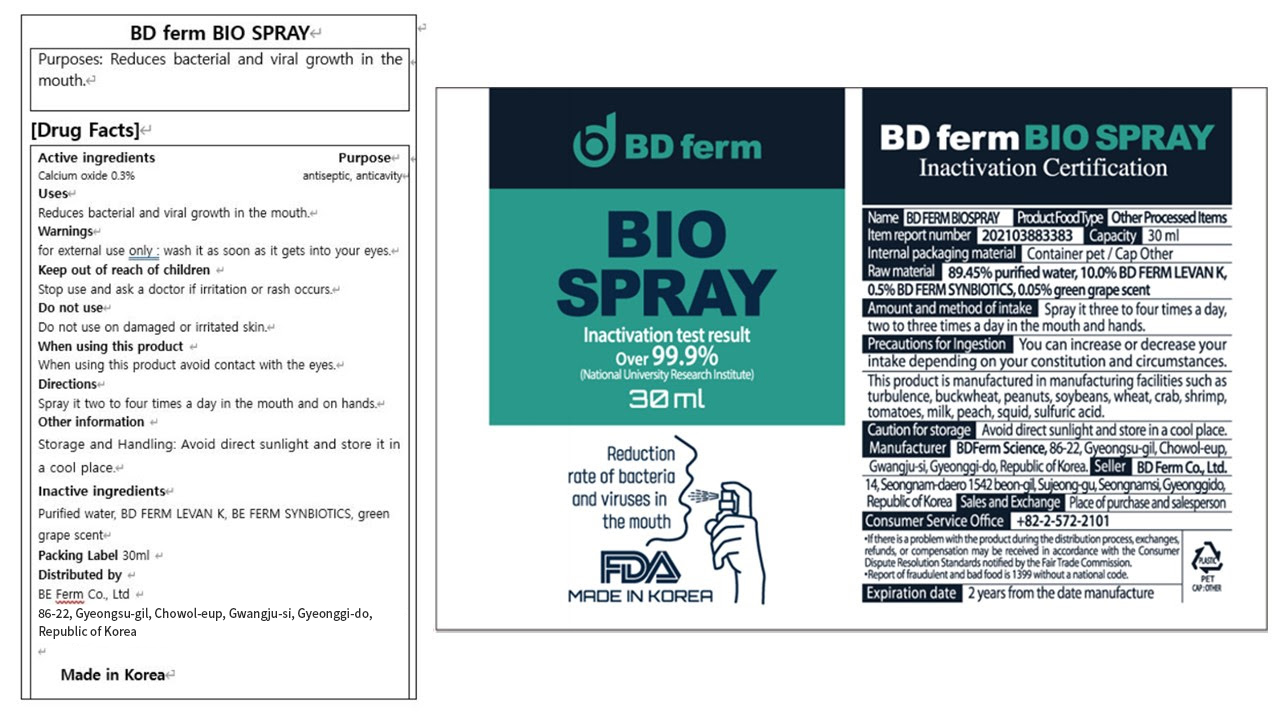 DRUG LABEL: BDFERM BIOSPRAY
NDC: 82332-102 | Form: SPRAY
Manufacturer: BDFERM CO.,ltd
Category: otc | Type: HUMAN OTC DRUG LABEL
Date: 20231227

ACTIVE INGREDIENTS: LIME (CALCIUM OXIDE) 0.295 g/100 mL
INACTIVE INGREDIENTS: WATER; SUCROSE; BACILLUS SUBTILIS; LACTOBACILLUS ACIDOPHILUS; ASPERGILLUS FLAVUS VAR. ORYZAE; SACCHAROMYCES CEREVISIAE

82332-102 BDFERM BIO SPRAY

Active Ingredients

Calcium Oxide 0.295%

Purposes

Reduces bacterial and viral growth in the mouth.

Uses

Spray it two to four times a day in the mouth and on hands.

Storage and Handling

Avoid direct sunlight and store it in a cool place.

Inactive Ingredients

Purified water, BD FERM LEVAN K, BE FERM SYNBIOTICS, green grape scent

Directions

Spray it two to four times a day in the mouth and on hands.

warnings

for external use only : wash it as soon as it gets into your eyes.

Warnings

Stop use and ask a doctor if irritation or rash occurs.

Warnings

Do not use on damaged or irritated skin.

Warnings

Keep out of reach of children.

When using

When using this product avoid contact with the eyes.